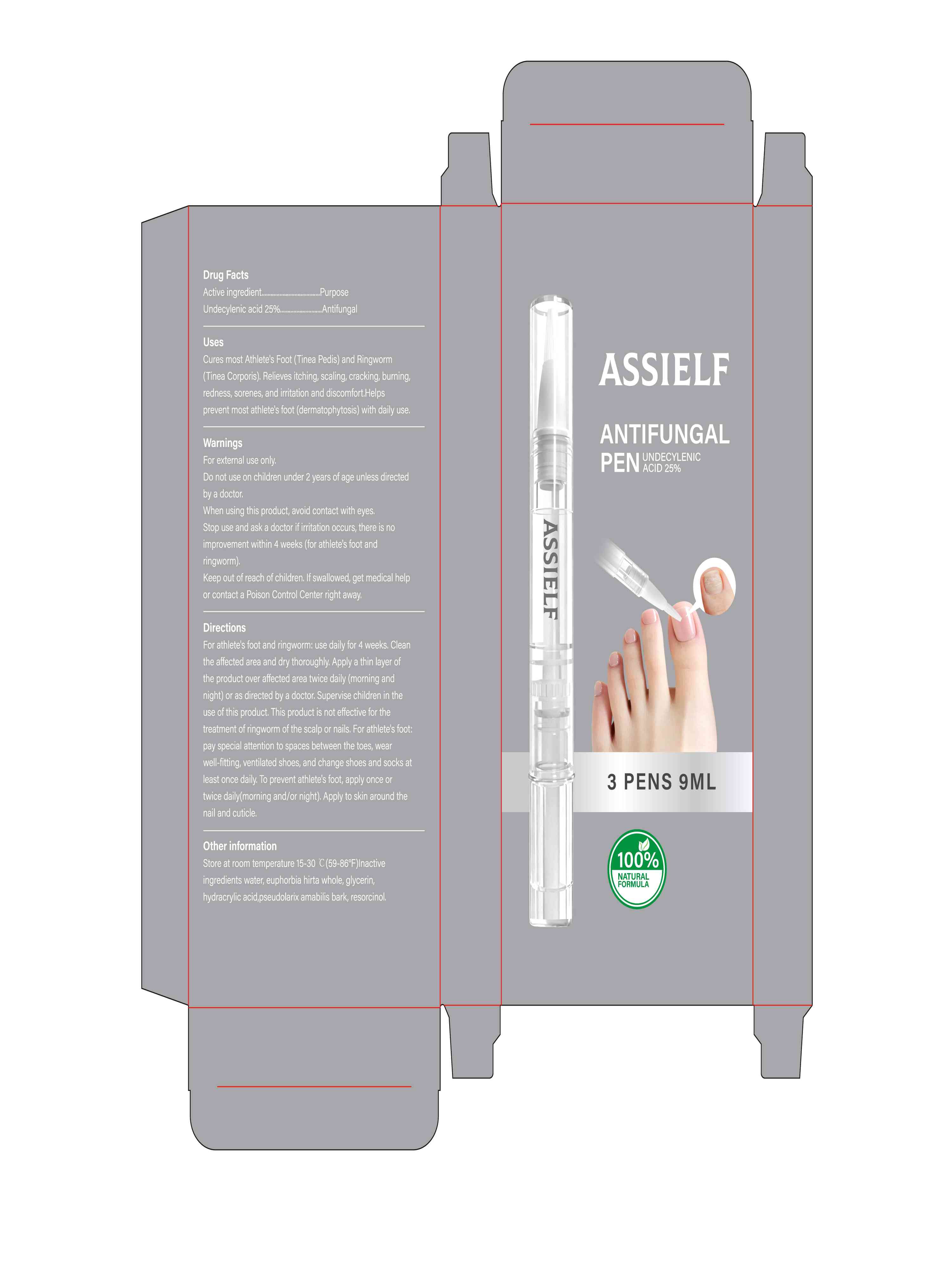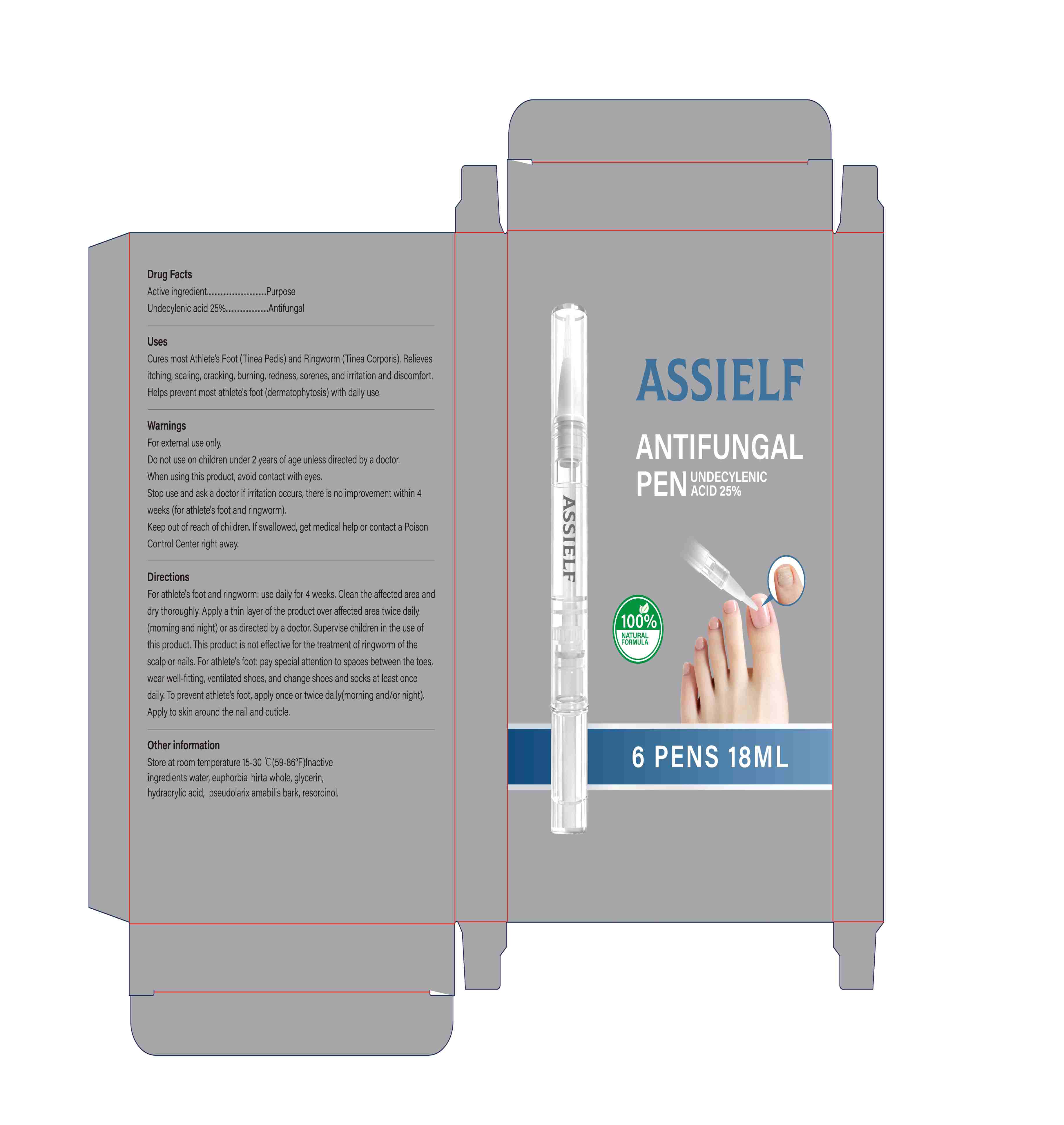 DRUG LABEL: ASSIELF ANTIFUNGAL PEN
NDC: 87418-002 | Form: LIQUID
Manufacturer: Shenzhen Yuanbang International Logistics Co., Ltd
Category: otc | Type: HUMAN OTC DRUG LABEL
Date: 20260208

ACTIVE INGREDIENTS: UNDECYLENIC ACID 25 g/100 mL
INACTIVE INGREDIENTS: RESORCINOL; EUPHORBIA HIRTA WHOLE; WATER; HYDRACRYLIC ACID; PSEUDOLARIX AMABILIS BARK; GLYCERIN

87418-002 ASSIELF ANTIFUNGAL PEN

Active ingredient......PurposeUndecylenic acid 25%.........Antifungal

PURPOSE

Cures most Athlete's Foot (Tinea Pedis) and Ringworm(Tinea Corporis). Relieves itching, scaling, cracking, burning,redness, sorenes, and irritation and discomfort.Helpsprevent most athlete's foot (dermatophytosis) with daily use.

WARNINGS

Store at room temperature 15-30 C (59-86°F）

Keep out of reach of children. If swallowed, get medical helpor contact a Poison Control Center right away.

INDICATIONS AND USAGE

For external use only.
Do not use on children under 2 years of age unless directedby a doctor.
When using this product, avoid contact with eyes.Stop use and ask a doctor if irritation occurs, there is noimprovement within 4 weeks (for athlete's foot andringworm).

Directions
For athlete's foot and ringworm: use daily for 4 weeks. Cleanthe affected area and dry thoroughly. Apply a thin layer ofthe product over affected area twice daily (morning andnight) or as directed by a doctor. Supervise children in theuse of this product. This product is not effective for thetreatment of ringworm of the scalp or nails. For athlete's foot:pay special attention to spaces between the toes, wearwell-fitting, ventilated shoes, and change shoes and socks atleast once daily. To prevent athlete's foot, apply once ortwice daily(morning and/or night). Apply to skin around thenail and cuticle.

INACTIVE INGREDIENT

water, euphorbia hirta whole, glycerin,hydracrylic acid,pseudolarix amabilis bark, resorcinol.